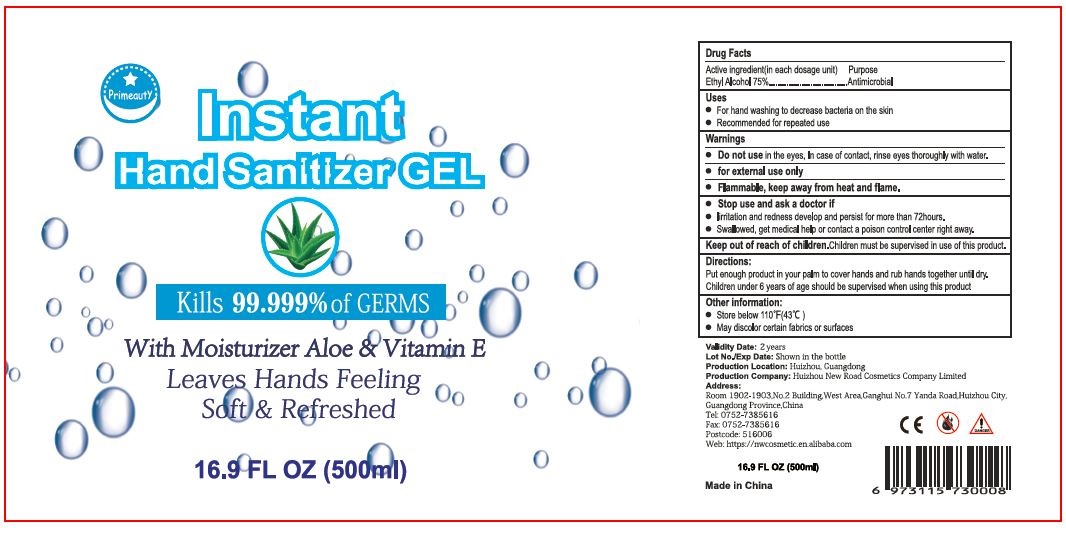 DRUG LABEL: Primeauty
NDC: 75186-004 | Form: LIQUID
Manufacturer: Huizhou Duomei Daily Necessities Co., Ltd.
Category: otc | Type: HUMAN OTC DRUG LABEL
Date: 20200817

ACTIVE INGREDIENTS: ALCOHOL 75 L/100 L
INACTIVE INGREDIENTS: GLYCERIN; WATER; ALOE VERA LEAF; CARBOMER HOMOPOLYMER, UNSPECIFIED TYPE; ALPHA-TOCOPHEROL ACETATE

Primeauty (HDPE Barrel w/ Screw Cap)

Active Ingredient(s)

Ethyl Alcohol 75% Purpose: Antimicrobial

Purpose

Antimicrobial

Uses

- For hand washing to decrease bacteria on the skin
- Recommended for repeated use

Warnings

- Do not use in the eyes. In case of contact, rinse eyes thoroughly with water.
- for external use only.
- Flammable, keep away from heat and flame

- Stop use and ask a doctor if
- irritation and redness develop and persist for more than 72 hours
- Swallowed, get medical help or contact a poison control center right away.

Keep out of reach of children. Children must be supervised in use of this product.

Directions

- Put enough product on hands to cover all surfaces. Rub hands together until dry.
- Children under 6 years of age should be supervised when using this product.

Other information

- Store below 110F (43C)
- May discolor certain fabrics or surfaces

Inactive ingredients

Water, Glycerin, Carbomer, Triethanolamine, Tocopheryl Acetate, Aloe